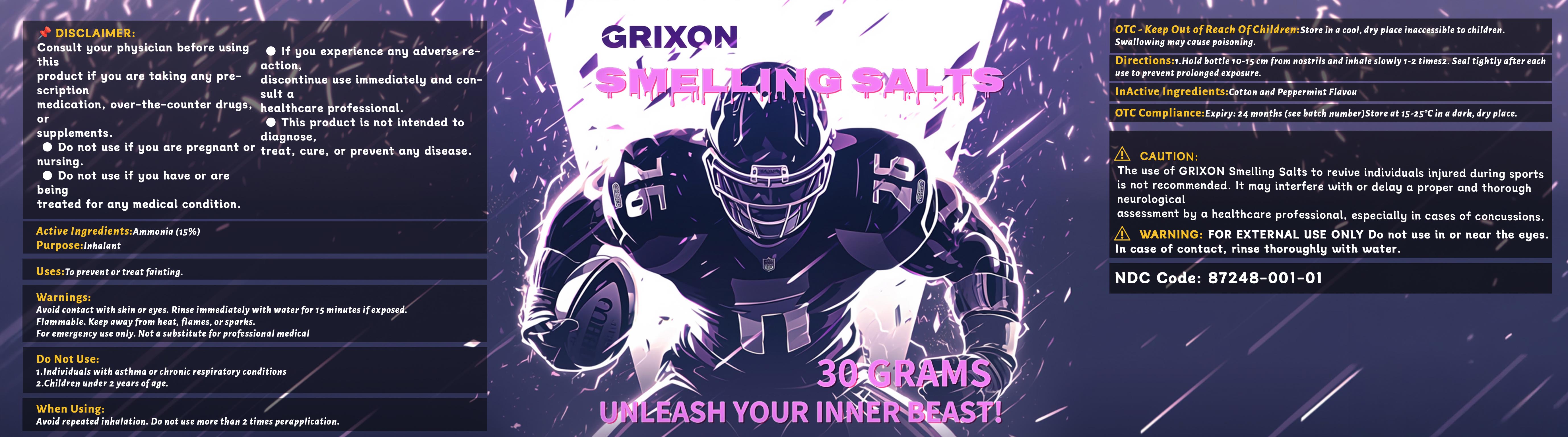 DRUG LABEL: Smelling Salt
NDC: 87248-001 | Form: GRANULE
Manufacturer: Shenzhen Jufeng Qisheng Technology Co., Ltd.
Category: otc | Type: HUMAN OTC DRUG LABEL
Date: 20251211

ACTIVE INGREDIENTS: AMMONIA 4.5 g/30 g
INACTIVE INGREDIENTS: PEPPERMINT; COTTON

87248-001 Smelling Salt

ACTIVE INGREDIENT

Ammonia 15%

PURPOSE

Inhalant

INDICATIONS AND USAGE

Uses:To preventor treat fainting

WARNINGS

Avoid contact with skin or eyes. Rinse immediately with water for 15 minutes ifexposed.
Flammable.Keep away from heat, flames, or sparks.
For emergency use only. Not a substitute for professional medical

DO NOT USE

1.Individuals with asthma or chronic respiratory conditions
2.Children under 2 years ofage.

WHEN USING

Avoid repeated inhalation. Do not use more than 2 times perapplication.

If you experience discomfort, please stop using.

KEEP OUT OF REACH OF CHILDREN

OTC- Keep Out ofReach OfChildren:Store in a cool, dry place inaccessible to children. Swallowing may cause poisoning

DOSAGE AND ADMINISTRATION

Directions:1.Hold bottle 10-15 cm from nostrils and inhale slowly 1-2 times2. Seal tightly after each
use to prevent prolonged exposure..

INACTIVE INGREDIENT

Cotton
Peppermint Flavour